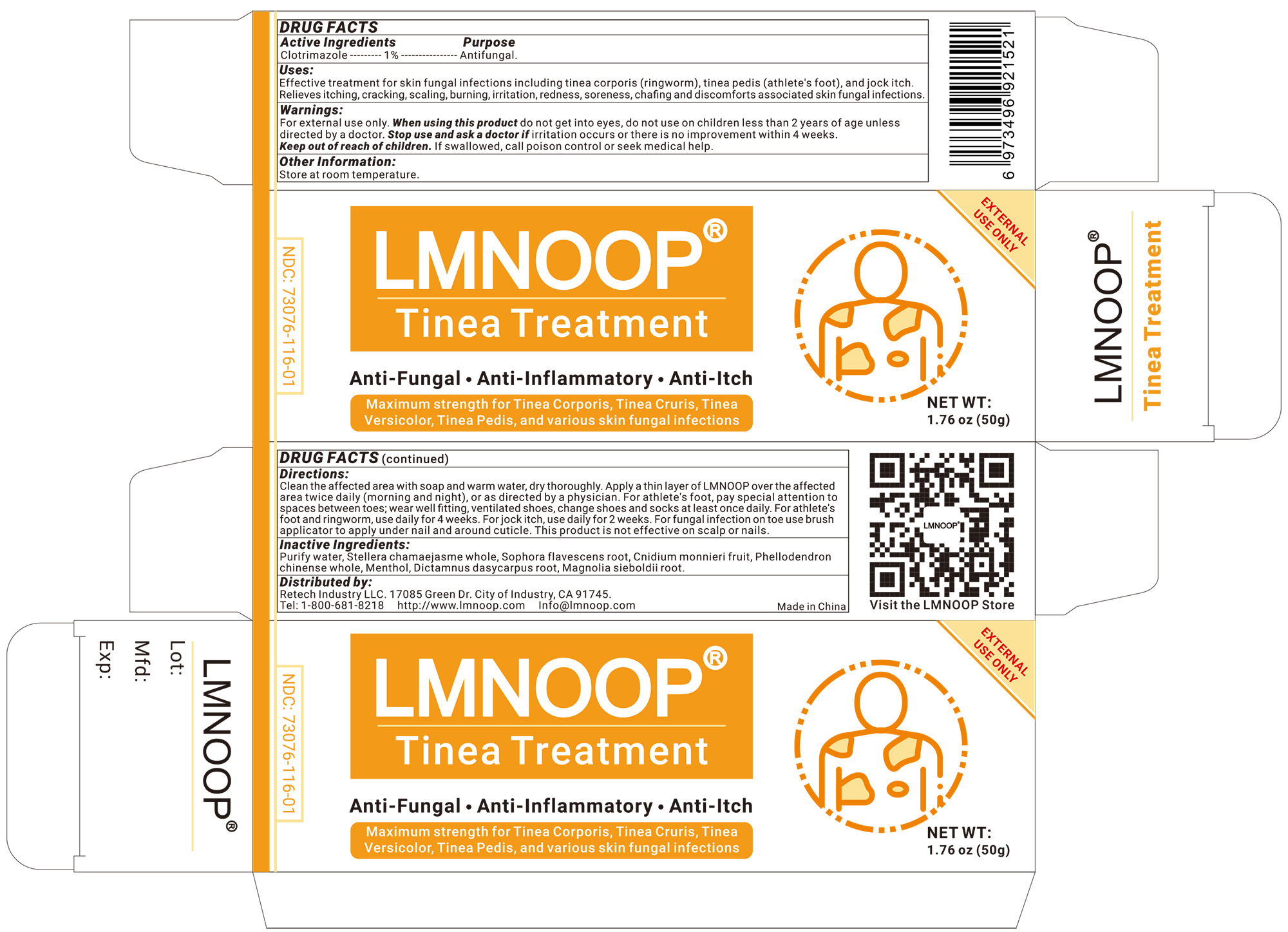 DRUG LABEL: LMNOOP Tinea Treatment
NDC: 73076-200 | Form: CREAM
Manufacturer: Shenzhen Ishan Technology Co., Ltd
Category: homeopathic | Type: HUMAN OTC DRUG LABEL
Date: 20260213

ACTIVE INGREDIENTS: OATMEAL 1 g/100 g
INACTIVE INGREDIENTS: SOPHORA FLAVESCENS ROOT 5 g/100 g; STELLERA CHAMAEJASME WHOLE 3 g/100 g; MENTHOL 1 g/100 g; DICTAMNUS DASYCARPUS ROOT 3 g/100 g; PHELLODENDRON CHINENSE WHOLE 5 g/100 g; MAGNOLIA SIEBOLDII ROOT 3 g/100 g; CNIDIUM MONNIERI FRUIT 3 g/100 g; WATER

Active Ingredient

Clotrimazole----1%----Antifungal

Inactive Ingredients

Purify water, stellera chamaejasme whole, sophora flavescens root, cnidium monnieri fruit, phellodendron chinense whole, Menthol, dictamnus dasycarpus root, Magnolia Sieboldii Root

Keep out of reach of children

if swallowed, call poison control or seek medical help.

ask a doctor

if irritation occurs or there is no improvement of athlete's foot or ringworm within 4 weeks or jock intch with 2 weeks

Stop use and ask a doctor

if irritation occurs or there is no improvement of athlete's foot or ringworm within 4 weeks or jock intch with 2 weeks.

USES

Effective treatment for skin fungal infections including tinea corporis (ringworm), tinea pedis (athlete's foot), and jock itch.
Relieves itching, cracking, scaling, burning, irritation, redness, soreness, chafing and discomforts associated skin fungal infections.

Other information

Store at room temperature.

Directions

Clean the affected area with soap and warm water, dry thoroughly. Apply a thin layer of LMNOOP over the affected area twice daily (morning and night), or as directed by a physician. For athlete's foot, pay special attention to spaces between toes; wear well fitting, ventilated shoes, change shoes and socks at least once daily. For athlete's foot and ringworm, use daily for 4 weeks. For jock itch, use daily for 2 weeks. For fungal infection on toe use brush applicator to apply under nail and around cuticle. This product is not effective on scalp or nails.

Dosage and administration

Apply as needed

When using this product

do not get into eyes

warning

For external use only. Ask a doctor before use if you have a condition that covers a large area of the body. When Using this product do not get into eyes. Do not use on nails or scalp & near the mouth or the eyes area. Stop use and ask a doctor if condition worsens or does not improve after regular use of this products as directed. Ask a doctor before using on children under 2 years of age. Keep out of reach of children. if swallowed, get medical help or contact a Poison Control Center right away.